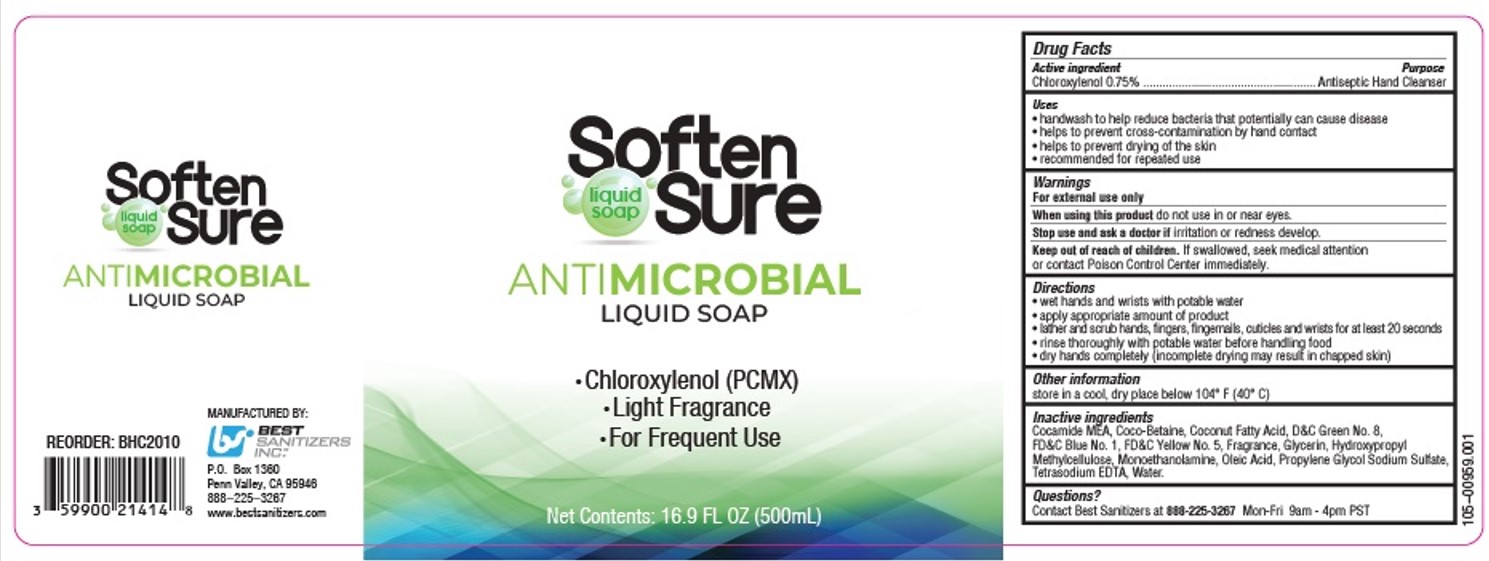 DRUG LABEL: SoftenSure Antimicrobial Liquid
NDC: 59900-217 | Form: LIQUID
Manufacturer: Best Sanitizers, Inc
Category: otc | Type: HUMAN OTC DRUG LABEL
Date: 20241213

ACTIVE INGREDIENTS: CHLOROXYLENOL 0.75 mg/100 mL
INACTIVE INGREDIENTS: GLYCERIN; COCAMIDE MEA; COCO-BETAINE; COCONUT ACID; WATER; FD&C YELLOW NO. 5; 2-AMINOETHANOL; HYDROXYPROPYL METHYLCELLULOSE; PROPYLENE GLYCOL; D&C GREEN NO. 8; FD&C BLUE NO. 1; OLEIC ACID; SODIUM SULFATE; TETRASODIUM EDTA

SoftenSure ALS 59900-217

Active ingredient

Chloroxylenol 0.75%

Purpose

Antiseptic Hand Cleanser

Uses

• handwash to help reduce bacteria that potentially can cause disease

• helps to prevent cross-contamination by hand contact

• helps to prevent drying of the skin

• recommended for repeated use

Warnings

For external use only

When using this product do not use in or near eyes.

Stop use and ask a doctor if irritation or redness develop.

Keep out of reach of children. If swallowed, seek medical attention or contact Poison Control Center immediately.

Directions

• wet hands and wrists with potable water

• apply appropriate amounts of product

• lather and scrub hands, fingers, fingernails, cuticles, and wrists for at least 20 seconds

• rinse thoroughly with potable water before handling food

• dry hands completely (incomplete drying may result in chapped skin)

Other information

store in a cool, dry place below 104° F (40° C)

Inactive ingredients

Cocamide MEA, Coco-Betaine, Coconut Fatty Acid, D&C Green No. 8, FD&C Blue No. 1, FD&C Yellow No. 5, Fragrance, Glycerin, Hydroxypropyl Methylcellulose, Monoethanolamine, Oleic Acid, Propylene Glycol, Sodium Sulfate, Tetrasodium EDTA, Water.

Questions?

Contact Best Sanitizers at 888-225-3267 Mon-Fri 9am - 4 pm PST

PACKAGE LABEL

liquid

soap

Soften

Sure

ANTIMICROBIAL

LIQUID SOAP

• Chloroxylenol (PCMX)

• Light Fragrance

• For Frequent Use

Net Contents: 16.9 FL OZ (500mL)